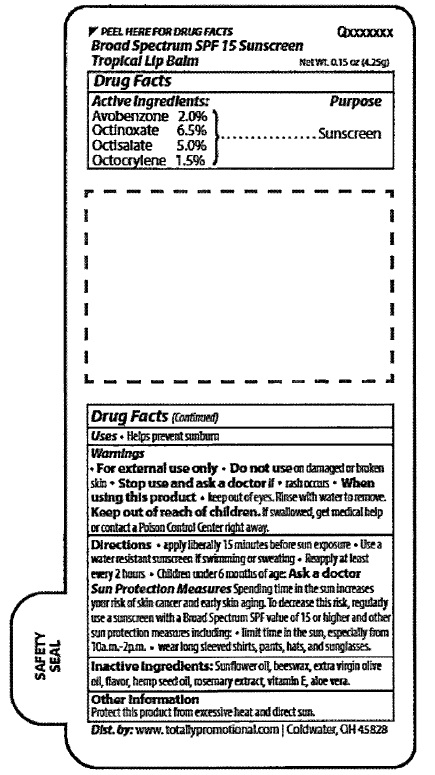 DRUG LABEL: Tropical Lip Balm
NDC: 71087-111 | Form: STICK
Manufacturer: Casad Company Inc.
Category: otc | Type: HUMAN OTC DRUG LABEL
Date: 20250103

ACTIVE INGREDIENTS: AVOBENZONE 2.0 g/100 g; OCTINOXATE 6.5 g/100 g; OCTISALATE 5.0 g/100 g; OCTOCRYLENE 1.5 g/100 g
INACTIVE INGREDIENTS: SUNFLOWER OIL; YELLOW WAX; OLIVE OIL; CANNABIS SATIVA SEED OIL; ROSEMARY OIL; .ALPHA.-TOCOPHEROL; ALOE VERA LEAF

Tropical Lip Balm

Drug Facts

Active Ingredients:
Avobenzone 2.0%
Octinoxate 6.5%
Octisalate 5.0%
Octocrylene 1.5%

Purpose
Avobenzone ,,,,Sunscreen
Octinoxate ,,,,,,,Sunscreen
Octisalate ,,,,,,,,Sunscreen
Octocrylene ,,,,,Sunscreen

INDICATIONS AND USAGE

Uses: Helps prevent sunburn

Warnings
• For external use only • Do not use on damaged or broken
skin • Stop use and ask a doctor if• rash occurs • When
using this product • keep out of eyes. Rinse with water to remove.

Keep out of reach of children: If swallowed, get medilcal
help or contact a Poison Control center right away.

DOSAGE AND ADMINISTRATION

Directions • Apply liberally 15 minutes before sun exposure • Use a
water resistant sunscreen if swimming or sweating • Reapply at least
every 2 hours • Children under 6 months of age: Ask a doctor

Sun Protection Measures Spending time in the sun increases your
risk of skin cancer and early skin aging. To decrease this risk, regularly
use a sunscreen with a Broad Spectrum SPF value of 15 or higher and
other protection measures including: • limit time in the sun, especially from
10a.m. - 2p.m.• wear long sleeved shirts, pants, hat, and sunglasses

Inactive ingredients: Sunflower oil, beeswax, extra virgin olive
oil, flavor, hemp seed oil, rosemary extract, vitamin E, aloe vera.

Other Information:

Protect this product from excessive heat and direct sun.

PACKAGE LABEL

Broad Spectrum SPF 15 Sunscreen
Tropical Lip Balm

Net Wt. 0.15 oz (4.25g)

SAFETY SEAL

Dist. by:www.totallypromotional.com | CoIdwater, OH 45828

res